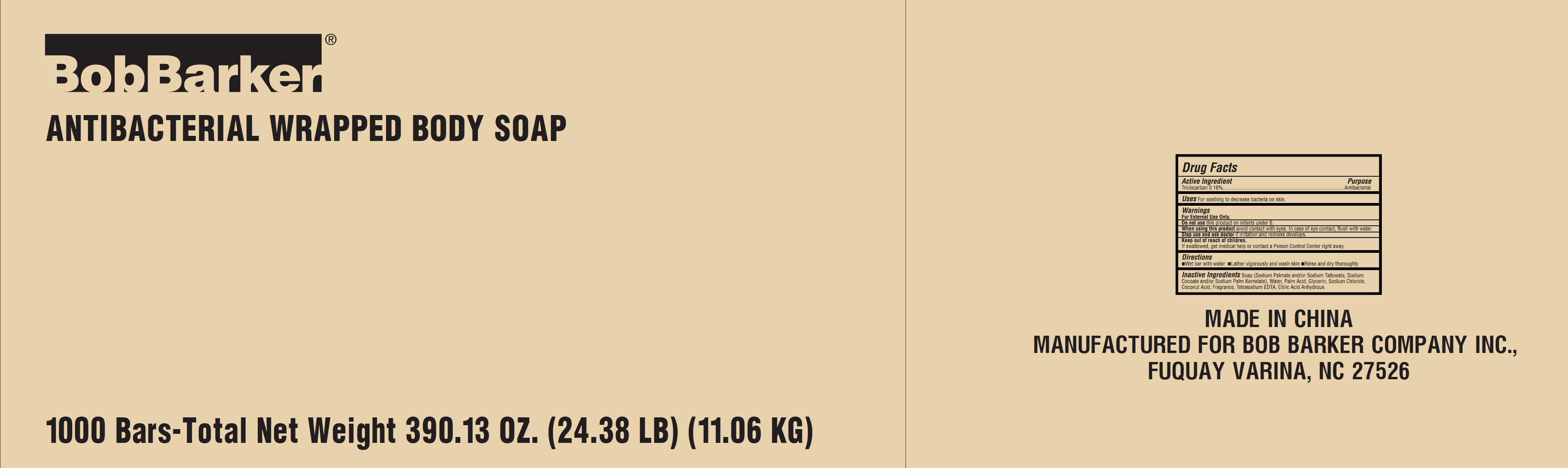 DRUG LABEL: bobbarker antibacterial bar
NDC: 69688-104 | Form: SOAP
Manufacturer: Jiangsu Xinheyuan Plastic Daily Chemical Co., Ltd.
Category: otc | Type: HUMAN OTC DRUG LABEL
Date: 20160726

ACTIVE INGREDIENTS: TRICLOSAN 0.16 g/100 g
INACTIVE INGREDIENTS: WATER; SODIUM PALMATE; CALCIUM CARBONATE; GLYCERIN; SODIUM CHLORIDE; PALM ACID; COCONUT ACID

Active Ingredient

Triclosan 0.16%

Purpose

Antibacterial

Uses

for washing to decrease bacteria on the skin.

Warnings

For external use only.

When using this product

Avoid contact with eyes. In case of eye contact, flush with water.

Don't use this product on infants under 6.

Stop use and ask a doctor

If irritation and redness develops.

Keep out of reach of children.

If swallowed, get medical help or contact a Poison Control Center right away.

Directions

- wet bar with water
- lather vigorously and wash skin
- rinse and dry thoroughly.

Inactive Ingredients

Soap (Sodium Palmate and/or Sodium Tallowate, Sodium Cocoate and/or Sodium Palm Kernelate), Water, Palm Acid, glycerine, sodium chloride, Coconut Acid, Fragrance, Tetrasodium EDTA, Citric Acid Anhydrous